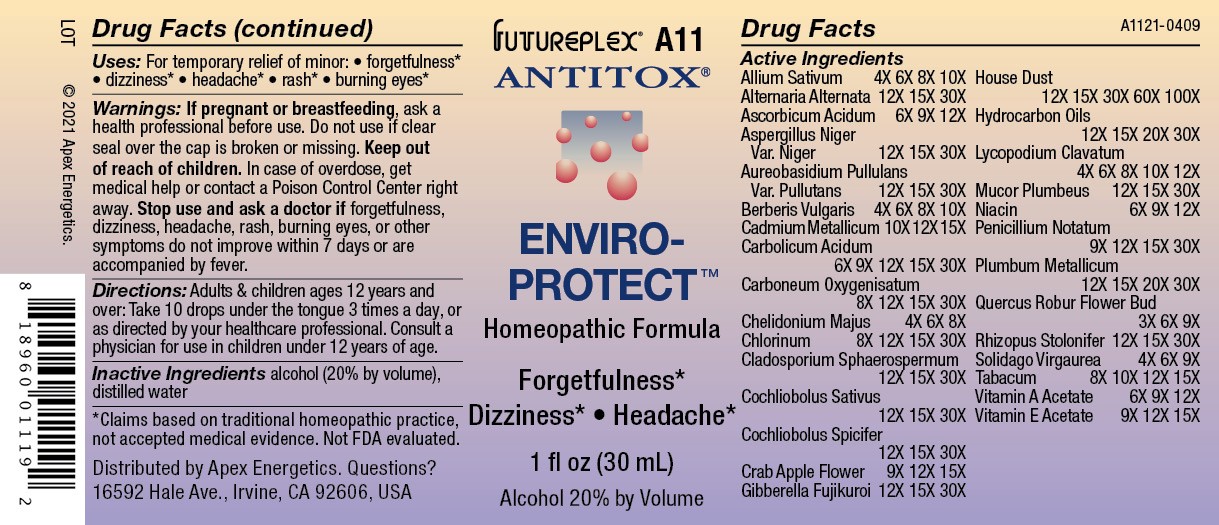 DRUG LABEL: A11
NDC: 63479-0111 | Form: SOLUTION/ DROPS
Manufacturer: Apex Energetics Inc.
Category: homeopathic | Type: HUMAN OTC DRUG LABEL
Date: 20240108

ACTIVE INGREDIENTS: MALUS SYLVESTRIS FLOWER 15 [hp_X]/1 mL; HOUSE DUST 100 [hp_X]/1 mL; BERBERIS VULGARIS ROOT BARK 10 [hp_X]/1 mL; CADMIUM 15 [hp_X]/1 mL; AUREOBASIDIUM PULLULANS VAR. PULLUTANS 30 [hp_X]/1 mL; PENICILLIUM CHRYSOGENUM VAR. CHRYSOGENUM 30 [hp_X]/1 mL; RHIZOPUS STOLONIFER 30 [hp_X]/1 mL; NIACIN 12 [hp_X]/1 mL; LEAD 30 [hp_X]/1 mL; QUERCUS ROBUR FLOWER BUD 9 [hp_X]/1 mL; SOLIDAGO VIRGAUREA FLOWERING TOP 9 [hp_X]/1 mL; VITAMIN A ACETATE 12 [hp_X]/1 mL; .ALPHA.-TOCOPHEROL ACETATE 15 [hp_X]/1 mL; TOBACCO LEAF 15 [hp_X]/1 mL; GARLIC 10 [hp_X]/1 mL; ASCORBIC ACID 12 [hp_X]/1 mL; PHENOL 30 [hp_X]/1 mL; ALTERNARIA ALTERNATA 30 [hp_X]/1 mL; CLADOSPORIUM SPHAEROSPERMUM 30 [hp_X]/1 mL; COCHLIOBOLUS SATIVUS 30 [hp_X]/1 mL; COCHLIOBOLUS SPICIFER 30 [hp_X]/1 mL; ASPERGILLUS NIGER VAR. NIGER 30 [hp_X]/1 mL; GIBBERELLA FUJIKUROI 30 [hp_X]/1 mL; MUCOR PLUMBEUS 30 [hp_X]/1 mL; CHELIDONIUM MAJUS 8 [hp_X]/1 mL; MINERAL OIL 30 [hp_X]/1 mL; LYCOPODIUM CLAVATUM SPORE 12 [hp_X]/1 mL; CARBON MONOXIDE 30 [hp_X]/1 mL; CHLORINE 30 [hp_X]/1 mL
INACTIVE INGREDIENTS: WATER; ALCOHOL

A11

Active Ingredients
Allium Sativum | 4X 6X 8X 10X
Alternaria Alternata | 12X 15X 30X
Ascorbicum Acidum | 6X 9X 12X
Aspergillus Niger Var. Niger | 12X 15X 30X
Aureobasidium Pullulans Var. Pullutans | 12X 15X 30X
Berberis Vulgaris | 4X 6X 8X 10X
Cadmium Metallicum | 10X 12X 15X
Carbolicum Acidum | 6X 9X 12X 15X 30X
Carboneum Oxygenisatum | 8X 12X 15X 30X
Chelidonium Majus | 4X 6X 8X
Chlorinum | 8X 12X 15X 30X
Cladosporium Sphaerospermum | 12X 15X 30X
Cochliobolus Sativus | 12X 15X 30X
Cochliobolus Spicifer | 12X 15X 30X
Crab Apple Flower | 9X 12X 15X
Gibberella Fujikuroi | 12X 15X 30X
House Dust | 12X 15X 30X 60X 100X
Hydrocarbon Oils | 12X 15X 20X 30X
Lycopodium Clavatum | 4X 6X 8X 10X 12X
Mucor Plumbeus | 12X 15X 30X
Niacin | 6X 9X 12X
Penicillium Notatum | 9X 12X 15X 30X
Plumbum Metallicum | 12X 15X 20X 30X
Quercus Robur Flower Bud | 3X 6X 9X
Rhizopus Stolonifer | 12X 15X 30X
Solidago Virgaurea | 4X 6X 9X
Tabacum | 8X 10X 12X 15X
Vitamin A Acetate | 6X 9X 12X
Vitamin E Acetate | 9X 12X 15X

INDICATIONS AND USAGE

Uses:

For temporary relief of minor:

forgetfulness*

dizziness*

headache*

rash*

burning eyes*

*Claims based on traditional homeopathic practice, not accepted medical evidence. Not FDA evaluated.

Warnings:

PREGNANCY OR BREAST FEEDING

If pregnant or breastfeeding, ask a health professional before use.

Do not use if clear seal over the cap is broken or missing.

Keep out of reach of children. In case of overdose, get medical help or contact a Poison Control Center right away.

Stop use and ask a doctor if forgetfulness, dizziness, headache, rash, burning eyes, or other symptoms do not improve within 7 days or are accompanied by fever.

Directions:

Adults & children ages 12 years and over: Take 10 drops under the tongue 3 times a day, or as directed by your healthcare professional. Consult a physician for use in children under 12 years of age.

Inactive Ingredients

alcohol (20% by volume), distilled water

Distributed by Apex Energetics. Questions?

16592 Hale Ave., Irvine, CA 92606, USA

PACKAGE LABEL

FUTUREPLEX® A11

ANTITOX®

ENVIRO-PROTECT™

Homeopathic Formula

Forgetfulness*

Dizziness* Headache*

1 fl oz (30 mL)

Alcohol 20% by Volume